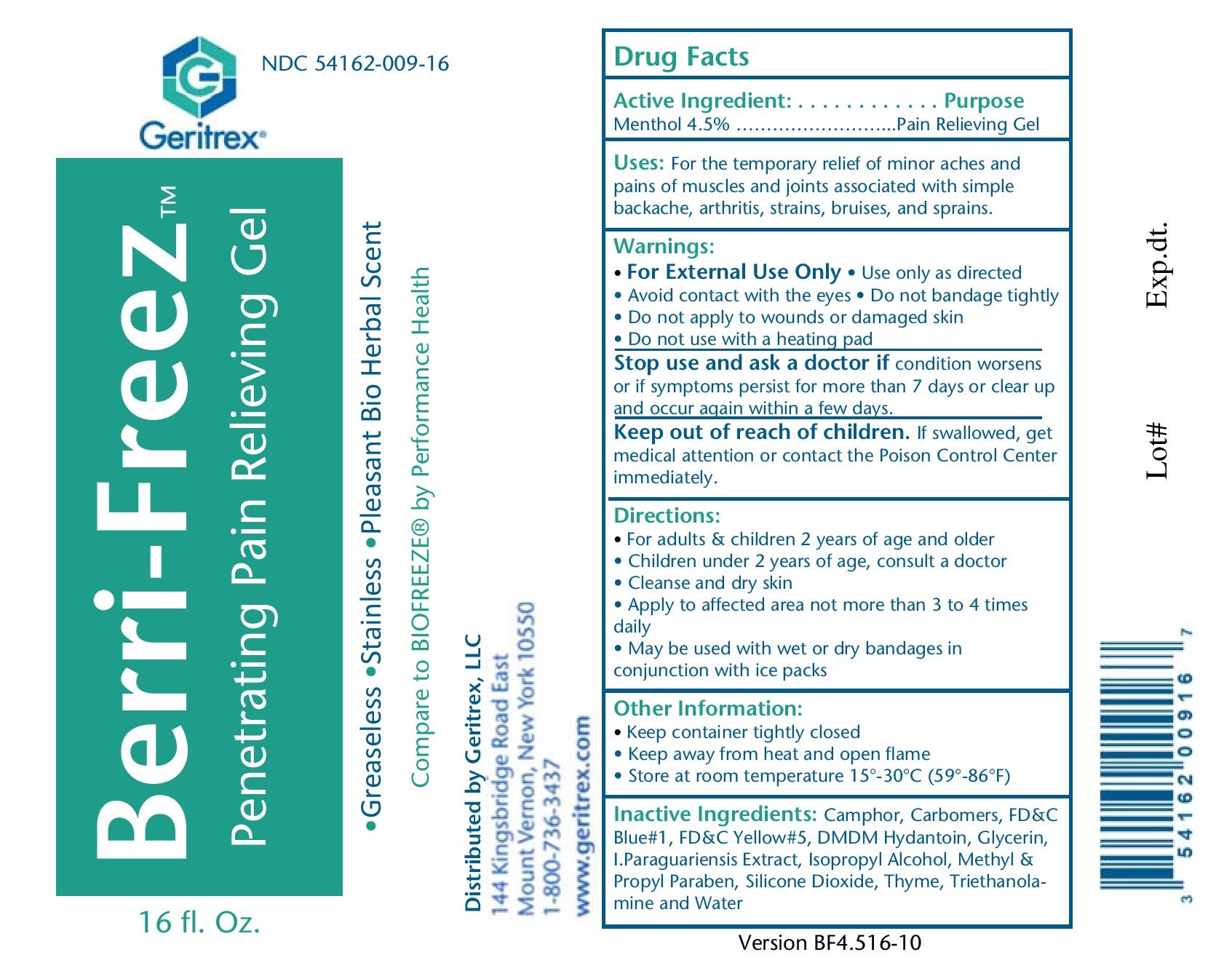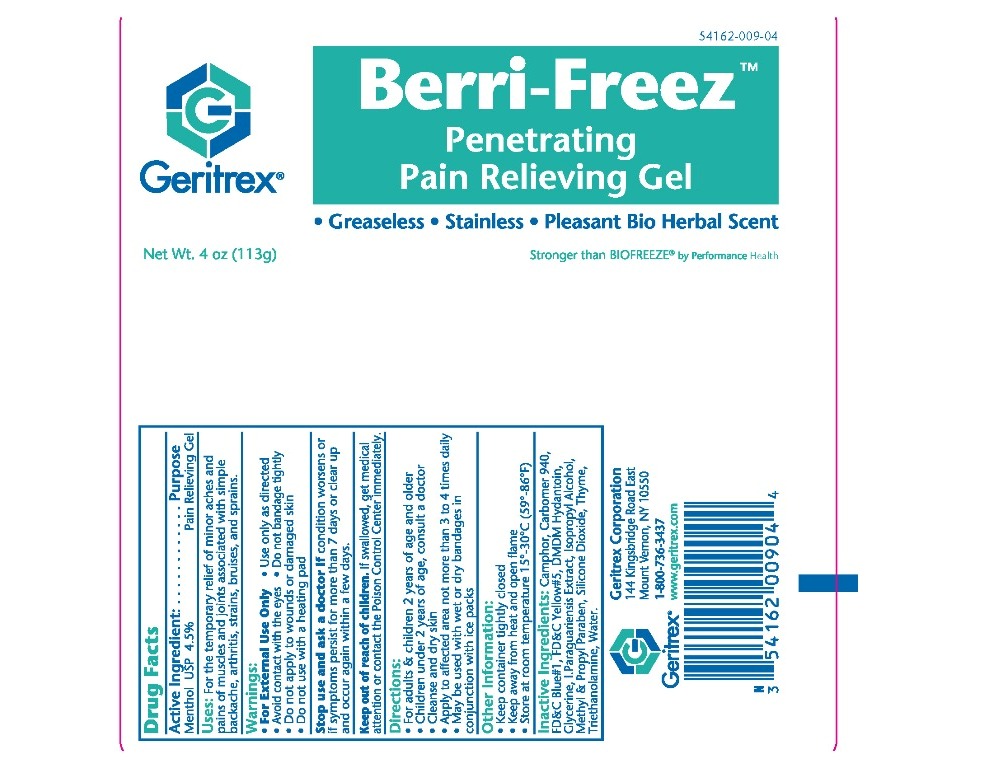 DRUG LABEL: Berri-Freez
NDC: 54162-009 | Form: GEL
Manufacturer: Geritrex LLC
Category: otc | Type: HUMAN OTC DRUG LABEL
Date: 20161020

ACTIVE INGREDIENTS: MENTHOL 5.085 g/113 g
INACTIVE INGREDIENTS: CAMPHOR (SYNTHETIC); CARBOMER 940; FD&C BLUE NO. 1; FD&C YELLOW NO. 5; DMDM HYDANTOIN; GLYCERIN; ILEX PARAGUARIENSIS LEAF; ISOPROPYL ALCOHOL; METHYLPARABEN; PROPYLPARABEN; SILICON DIOXIDE; THYME; TROLAMINE; WATER

Berri-Freez

Drug Facts

Active Ingredient Purpose

Menthol USP 4.5% Pain Relieving Gel

Uses

For the temporary relief of minor aches and

pains of muscles and joints associated with simple

backache, arthritis, strains, bruises, and sprains

Directions

For adults or children 2 years of age and older

Children under 2 years of age, consult a doctor

Cleanse and dry skin

Apply to affected area not more than 3 to 4 times daily

May be used with wet or dry bandages in conjunction with ice packs

Keep container tightly closed

DOSAGE AND ADMINISTRATION

Apply to affected area not more than 3 to 4 times daily

Warnings

For External Use Only Use only as directed

Avoid contact with the eyes. Do not bandage tightly

Do not apply to wounds or damaged skin

Do not use with a heating pad

Stop use and ask a doctor if condition worsens or if

symptoms persist for more than 7 days or clear up

and occur again within a few days

Inactive Ingredients

Camphor, Carbomer 940, FD&C Blue#1, FD&C Yellow#5

DMDM Hydantoin, Glycerine, I.paraguariensis Extract, Isopropyl Alcohol

Methyl & Propyle paraben, Silicon Dioxide, Thyme, Triethanolamine, water

STORAGE AND HANDLING

Keep away from heat and open flame

Store at room temperature 15°-30°C (59°-86°F)

Keep out of reach of children if swallowed, get medical

attention or contact the poison control center immediately